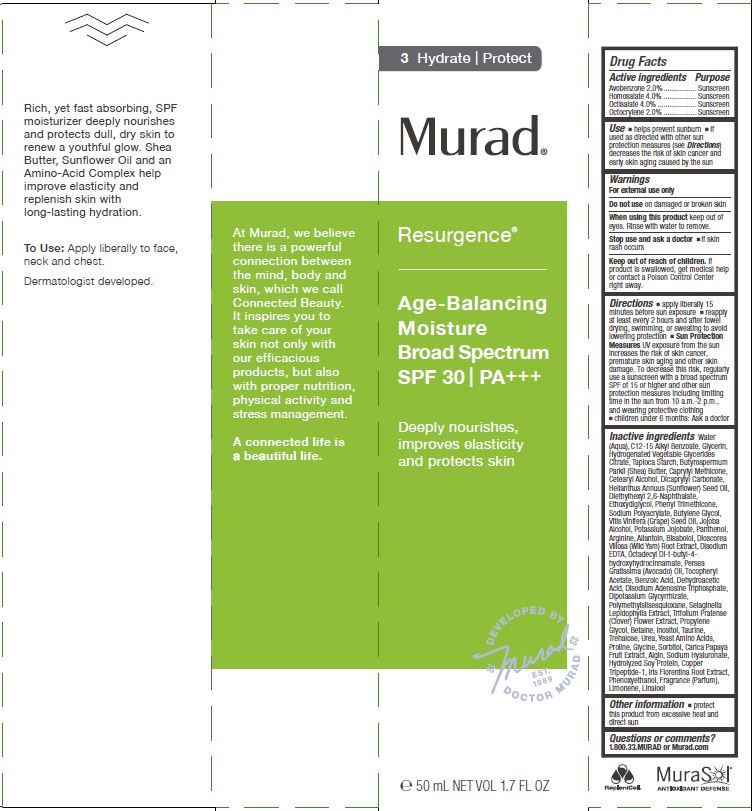 DRUG LABEL: MURAD - RESURGENCE - AGE-BALANCING MOISTURE 
NDC: 70381-106 | Form: CREAM
Manufacturer: Murad, LLC
Category: otc | Type: HUMAN OTC DRUG LABEL
Date: 20201227

ACTIVE INGREDIENTS: AVOBENZONE 2 g/100 mL; HOMOSALATE 4 g/100 mL; OCTISALATE 4 g/100 mL; OCTOCRYLENE 2 g/100 mL
INACTIVE INGREDIENTS: WATER; ALKYL (C12-15) BENZOATE; GLYCERIN; HYDROGENATED COCO-GLYCERIDES; STARCH, TAPIOCA; SHEA BUTTER; CAPRYLYL TRISILOXANE; CETOSTEARYL ALCOHOL; DICAPRYLYL CARBONATE; SUNFLOWER OIL; DIETHYLHEXYL 2,6-NAPHTHALATE; DIETHYLENE GLYCOL MONOETHYL ETHER; PHENYL TRIMETHICONE; SODIUM POLYACRYLATE (8000 MW); BUTYLENE GLYCOL; GRAPE SEED OIL; POTASSIUM HYDROLYZED JOJOBA ESTERS; PANTHENOL; ARGININE; ALLANTOIN; .ALPHA.-BISABOLOL, (+)-; DIOSCOREA VILLOSA TUBER; EDETATE DISODIUM; OCTADECYL DI-TERT-BUTYL-4-HYDROXYHYDROCINNAMATE; AVOCADO OIL; .ALPHA.-TOCOPHEROL ACETATE; BENZOIC ACID; DEHYDROACETIC ACID; ADENOSINE TRIPHOSPHATE DISODIUM; GLYCYRRHIZINATE DIPOTASSIUM; POLYMETHYLSILSESQUIOXANE (4.5 MICRONS); SELAGINELLA LEPIDOPHYLLA WHOLE; TRIFOLIUM PRATENSE FLOWER; PROPYLENE GLYCOL; BETAINE; INOSITOL; TAURINE; TREHALOSE; UREA; AMINO ACIDS, SOURCE UNSPECIFIED; PROLINE; GLYCINE; SORBITOL; PAPAYA; SODIUM ALGINATE; HYALURONATE SODIUM; HYDROLYZED SOY PROTEIN (ENZYMATIC; 2000 MW); PREZATIDE COPPER; IRIS X GERMANICA NOTHOVAR. FLORENTINA ROOT; PHENOXYETHANOL; LIMONENE, (+)-; LINALOOL, (+)-

MURAD - RESURGENCE - AGE-BALANCING MOISTURE, BROAD SPECTRUM SPF 30

ACTIVE INGREDIENTS

Avobenzone 2.0%
Homosalate 6.5%
Octisalate 4.0%
Oxycrylene 2.0%

PURPOSE

SUNSCREEN

USES

- helps prevent sunburn
- if used as directed with other sun protection measures (see Directions) decreases the risk of skin cancer and early skin aging caused by the sun.

WARNINGS

For external use only

Do not use on damaged or broken skin

When using this product keep out of eyes. Rinse with water to remove.

Stop use and ask a doctor

- if skin rash occurs

Keep out of reach of children. If product is swallowed, get medical help or contact a Poison Control Center right away.

DIRECTIONS

- apply liberally 15 minutes before sun exposure
- use a water resistant sunscreen if swimming or sweating
- reapply at least every 2 hours
- Sun Protection Measures.pending time in the sun increases your risk of skin cancer and early skin aging. To decrease this risk, regularly use a sunscreen with a Broad Spectrum SPF value of 15 or higher and other sun protection measures including:
- limit time in the sun, especially from 10 a.m. - 2 p.m.
- wear long-sleeved shirts, pants, hats, and sunglasses.
- children under 6 months of age: ask a doctor

INACTIVE INGREDIENTS

Water
(Aqua), C12-15 Alkyl Benzoate, Glycerin, Hydrogenated Vegetable Glycerides Citrate, Tapioca Starch, Butyrospermum Parkii (Shea) Butter, Caprylyl Methicone, Cetearyl Alcohol, Dicaprylyl Carbonate, Helianthus Annuus (Sunflower) Seed Oil, Diethylhexyl 2,6-Naphthalate, Ethoxydiglycol, Phenyl Trimethicone, Sodium Polyacrylate, Butylene Glycol, Vitis Vinifera (Grape) Seed Oil, Jojoba Alcohol, Potassium Jojobate, Panthenol, Arginine, Allantoin, Bisabolol, Dioscorea Villosa (Wild Yam) Root Extract, Disodium EDTA, Octadecyl Di-t-butyl-4- hydroxyhydrocinnamate, Persea Gratissima (Avocado) Oil, Tocopheryl Acetate, Benzoic Acid, Dehydroacetic Acid, Disodium Adenosine Triphosphate, Dipotassium Glycyrrhizate, Polymethylsilsesquioxane, Selaginella Lepidophylla Extract, Trifolium Pratense (Clover) Flower Extract, Propylene Glycol, Betaine, Inositol, Taurine, Trehalose, Urea, Yeast Amino Acids, Proline, Glycine, Sorbitol, Carica Papaya Fruit Extract, Algin, Sodium Hyaluronate, Hydrolyzed Soy Protein, Copper Tripeptide-1, Iris Florentina Root Extract, Phenoxyethanol, Fragrance (Parfum), Limonene, Linalool

OTHER INFORMATION

- protect this product from excessive heat and direct sun

QUESTIONS OR COMMENTS?

1.800.33.MURAD or Murad.com